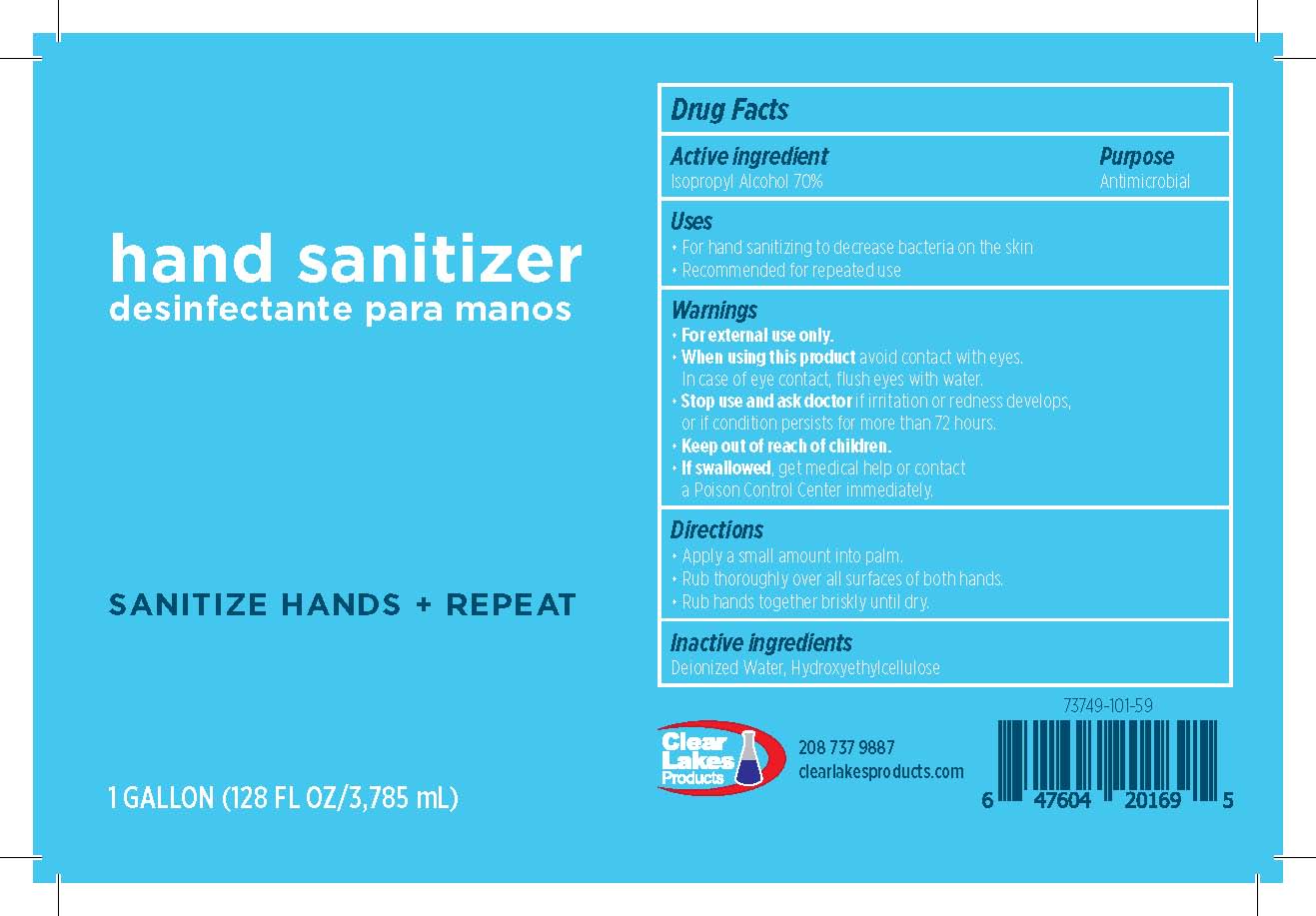 DRUG LABEL: Clear Lakes Products Hand Sanitizer
NDC: 73749-101 | Form: GEL
Manufacturer: Clear Lakes Products, LLC
Category: otc | Type: HUMAN OTC DRUG LABEL
Date: 20201231

ACTIVE INGREDIENTS: ISOPROPYL ALCOHOL 0.7 L/1 L
INACTIVE INGREDIENTS: WATER; HYDROXYETHYL CELLULOSE (4000 MPA.S AT 1%)

Active Ingredient

Isopropyl Alcohol 70%

Purpose

Antimicrobial

Uses

- For hand sanitizing to decrease bacteria on the skin
- Recommended for repeated use

Warnings

- For external use only.
- When using this product avoid contact with eyes. In case of eye contact, flush eyes with water.
- Stop use and ask doctor if irritation or redness develops, or if condition persists for more than 72 hours.
- Keep out of reach of children.
- If swallowed, get medical help or contact a Poison Control Center immediately.

Directions

- Pump a small amount into palm.
- Rub thoroughly over all surfaces of both hands.
- Rub hands together briskly until dry.

Inactive ingredients

Water, Hydroxyethylcellulose